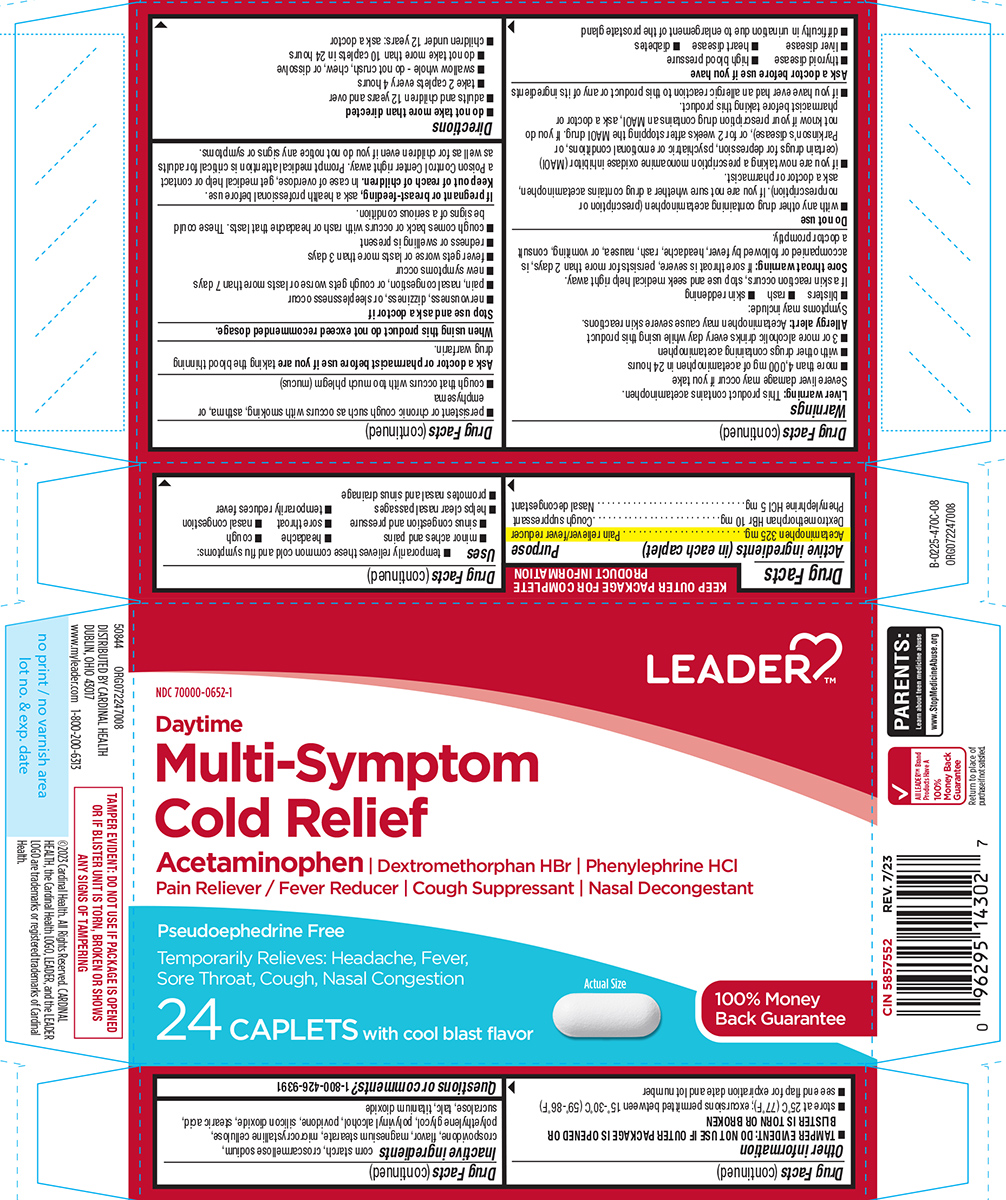 DRUG LABEL: Cold Relief
NDC: 70000-0652 | Form: TABLET, FILM COATED
Manufacturer: Cardinal Health 110, LLC. DBA Leader
Category: otc | Type: HUMAN OTC DRUG LABEL
Date: 20251028

ACTIVE INGREDIENTS: ACETAMINOPHEN 325 mg/1 1; DEXTROMETHORPHAN HYDROBROMIDE 10 mg/1 1; PHENYLEPHRINE HYDROCHLORIDE 5 mg/1 1
INACTIVE INGREDIENTS: STARCH, CORN; CROSCARMELLOSE SODIUM; CROSPOVIDONE, UNSPECIFIED; MAGNESIUM STEARATE; MICROCRYSTALLINE CELLULOSE; POLYETHYLENE GLYCOL, UNSPECIFIED; POLYVINYL ALCOHOL, UNSPECIFIED; POVIDONE, UNSPECIFIED; SILICON DIOXIDE; STEARIC ACID; SUCRALOSE; TALC; TITANIUM DIOXIDE

Leader 44-470C

Active ingredients (in each caplet)

Acetaminophen 325 mg
Dextromethorphan HBr 10 mg
Phenylephrine HCl 5 mg

Purpose

Pain reliever/fever reducer
Cough suppressant
Nasal decongestant

Uses

- temporarily relieves these common cold and flu symptoms:
  - minor aches and pains
  - headache
  - nasal congestion
  - cough
  - sore throat
  - sinus congestion and pressure
- temporarily reduces fever
- helps clear nasal passages
- promotes nasal and sinus drainage

Warnings

Liver warning: This product contains acetaminophen. Severe liver damage may occur if you take

- more than 4,000 mg of acetaminophen in 24 hours
- with other drugs containing acetaminophen
- 3 or more alcoholic drinks every day while using this product

Allergy alert: Acetaminophen may cause severe skin reactions. Symptoms may include:

- blisters
- rash
- skin reddening

If a skin reaction occurs, stop use and seek medical help right away.

Sore throat warning: If sore throat is severe, persists for more than 2 days, is accompanied or followed by fever, headache, rash, nausea, or vomiting, consult a doctor promptly.

Do not use

- with any other drug containing acetaminophen (prescription or nonprescription). If you are not sure whether a drug contains acetaminophen, ask a doctor or pharmacist.
- if you are now taking a prescription monoamine oxidase inhibitor (MAOI) (certain drugs for depression, psychiatric or emotional conditions, or Parkinson's disease), or for 2 weeks after stopping the MAOI drug. If you do not know if your prescription drug contains an MAOI, ask a doctor or pharmacist before taking this product.
- if you have ever had an allergic reaction to this product or any of its ingredients

Ask a doctor before use if you have

- liver disease
- diabetes
- heart disease
- thyroid disease
- high blood pressure
- difficulty in urination due to enlargement of the prostate gland
- persistent or chronic cough such as occurs with smoking, asthma, or emphysema
- cough that occurs with too much phlegm (mucus)

Ask a doctor or pharmacist before use if you are

taking the blood thinning drug warfarin.

When using this product

do not exceed recommended dosage.

Stop use and ask a doctor if

- nervousness, dizziness, or sleeplessness occur
- pain, nasal congestion, or cough gets worse or lasts more than 7 days
- fever gets worse or lasts more than 3 days
- redness or swelling is present
- new symptoms occur
- cough comes back or occurs with rash or headache that lasts. These could be signs of a serious condition.

If pregnant or breast-feeding,

ask a health professional before use.

Keep out of reach of children.

In case of overdose, get medical help or contact a Poison Control Center right away. Prompt medical attention is critical for adults as well as for children even if you do not notice any signs or symptoms.

Directions

- do not take more than directed
- adults and children 12 years and over
  - take 2 caplets every 4 hours
  - swallow whole - do not crush, chew, or dissolve
  - do not take more than 10 caplets in 24 hours
- children under 12 years: ask a doctor

Other information

- TAMPER EVIDENT: DO NOT USE IF OUTER PACKAGE IS OPENED OR BLISTER IS TORN OR BROKEN
- store at 25ºC (77ºF); excursions permitted between 15º-30ºC (59º-86ºF)
- see end flap for expiration date and lot number

Inactive ingredients

corn starch, croscarmellose sodium, crospovidone, flavor, magnesium stearate, microcrystalline cellulose, polyethylene glycol, polyvinyl alcohol, povidone, silicon dioxide, stearic acid, sucralose, talc, titanium dioxide

Questions or comments?

1-800-426-9391

Principal Display Panel

LEADER™

NDC 70000-0652-1

Daytime
Multi-Symptom
Cold Relief

Acetaminophen | Dextromethorphan HBr | Phenylephrine HCl
Pain Reliever / Fever Reducer | Cough Suppressant | Nasal Decongestant

Pseudoephedrine Free

Temporarily Relieves: Headache, Fever,
Sore Throat, Cough, Nasal Congestion

24 CAPLETS with cool blast flavor

Actual Size

100% Money
Back Guarantee

TAMPER EVIDENT: DO NOT USE IF PACKAGE IS OPENED
OR IF BLISTER UNIT IS TORN, BROKEN OR SHOWS
ANY SIGNS OF TAMPERING

PARENTS:
Learn about teen medicine abuse
www.StopMedicineAbuse.org

50844 ORG072247008

All LEADER™ Brand
Products Have A
100%
Money Back
Guarantee

Return to place of
purchase if not satisfied.

DISTRIBUTED BY CARDINAL HEALTH
DUBLIN, OHIO 43017
www.myleader.com 1-800-200-6313

©2023 Cardinal Health. All Rights Reserved. CARDINAL
HEALTH, the Cardinal Health LOGO, LEADER, and the LEADER
LOGO are trademarks or registered trademarks of Cardinal
Health.

CIN 5857552 REV. 7/23

Leader 44-470